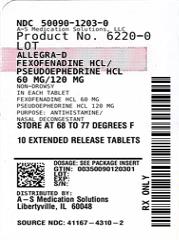 DRUG LABEL: ALLEGRA-D
NDC: 50090-1203 | Form: TABLET, FILM COATED, EXTENDED RELEASE
Manufacturer: A-S Medication Solutions
Category: otc | Type: HUMAN OTC DRUG LABEL
Date: 20240107

ACTIVE INGREDIENTS: FEXOFENADINE HYDROCHLORIDE 60 mg/1 1; PSEUDOEPHEDRINE HYDROCHLORIDE 120 mg/1 1
INACTIVE INGREDIENTS: CARNAUBA WAX; SILICON DIOXIDE; CROSCARMELLOSE SODIUM; HYPROMELLOSE, UNSPECIFIED; MAGNESIUM STEARATE; MICROCRYSTALLINE CELLULOSE; POLYETHYLENE GLYCOL, UNSPECIFIED; STARCH, CORN; STEARIC ACID

ALLEGRA-D

Drug Facts

Active ingredients

(in each tablet)

Fexofenadine HCl 60 mg

Purpose

Antihistamine

Active ingredients

(in each tablet)

Pseudoephedrine HCl 120 mg

Purpose

Nasal decongestant

Uses

- temporarily relieves these symptoms due to hay fever or other upper respiratory allergies:
  ▪ runny nose
  ▪ sneezing
  ▪ itchy, watery eyes
  ▪ itching of the nose or throat
- temporarily relieves nasal congestion due to the common cold, hay fever or other upper respiratory allergies
- reduces swelling of nasal passages
- temporarily relieves sinus congestion and pressure
- temporarily restores freer breathing through the nose

Warnings

Do not use

- if you have ever had an allergic reaction to this product or any of its ingredients
- if you are now taking a prescription monoamine oxidase inhibitor (MAOI)
  (certain drugs for depression, psychiatric, or emotional conditions, or Parkinson’s disease), or for 2 weeks after stopping the MAOI drug. If you do not know if your prescription drug contains an MAOI, ask a doctor or pharmacist before taking this product.
- If you have difficulty swallowing

Ask a doctor before use if you have

- heart disease
- thyroid disease
- glaucoma
- high blood pressure
- diabetes
- trouble urinating due to an enlarged prostate gland
- kidney disease. Your doctor should determine if you need a different dose.

When using this product

- do not take more than directed
- do not take at the same time as aluminum or magnesium antacids
- do not take with fruit juices (see Directions)
- the tablet coating may be seen in the stool (this is normal). Continue to take as directed (see Directions).

Stop use and ask a doctor if

- an allergic reaction to this product occurs. Seek medical help right away.
- symptoms do not improve within 7 days or are accompanied by a fever
- you get nervous, dizzy, or sleepless

If pregnant or breast-feeding,

ask a health professional before use.

Keep out of reach of children.

In case of overdose, get medical help or contact a Poison Control Center right away.

Directions

- do not divide, crush, chew or dissolve the tablet; swallow tablet whole

adults and children 12 years of age and over | take 1 tablet with a glass of water every 12 hours on an empty stomach; do not take more than 2 tablet in 24 hours
children under 12 years of age | do not use
adults 65 years of age and older | ask a doctor
consumers with kidney disease | ask a doctor

Other information

- safety sealed: do not use if carton is opened or if individual blister units are torn or opened
- store between 20º and 25ºC (68º and 77ºF)

Inactive ingredients

carnauba wax, colloidal silicon dioxide, croscarmellose sodium, hypromellose, magnesium stearate, microcrystalline cellulose, polyethylene glycol, pregelatinized starch, stearic acid

Questions or comments?

call toll-free 1-800-633-1610 or www.allegra.com

HOW SUPPLIED

Product: 50090-1203

NDC: 50090-1203-0 10 TABLET, FILM COATED, EXTENDED RELEASE in a BLISTER PACK / 1 in a CARTON